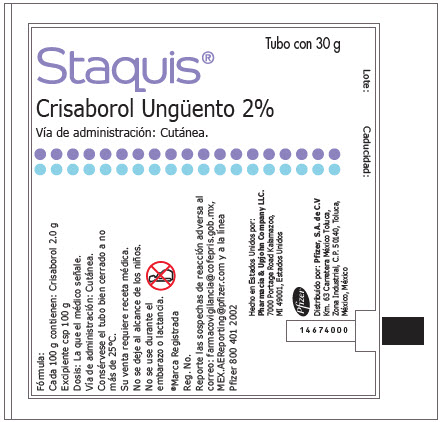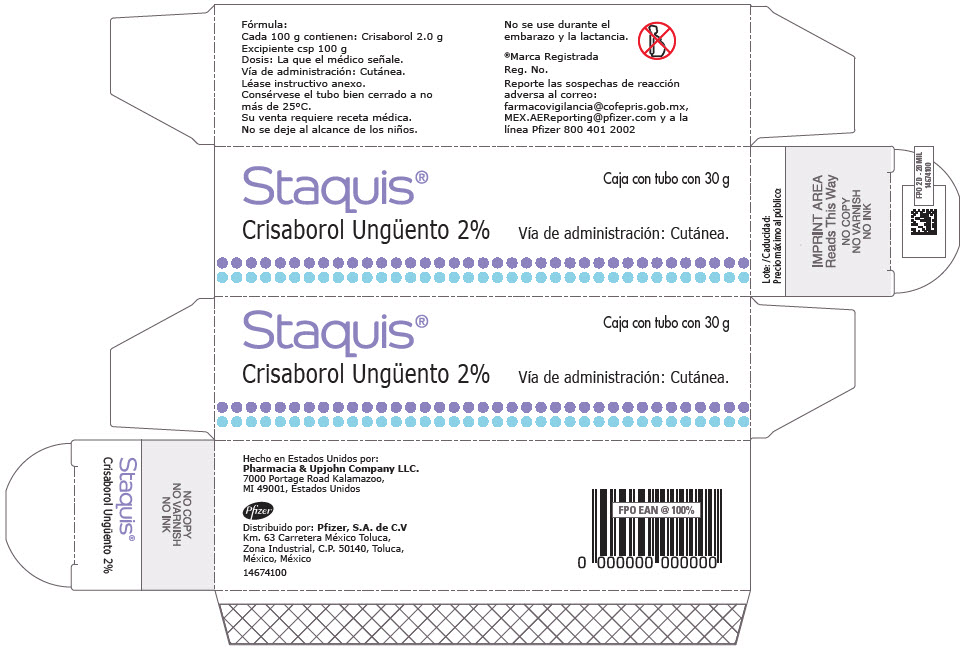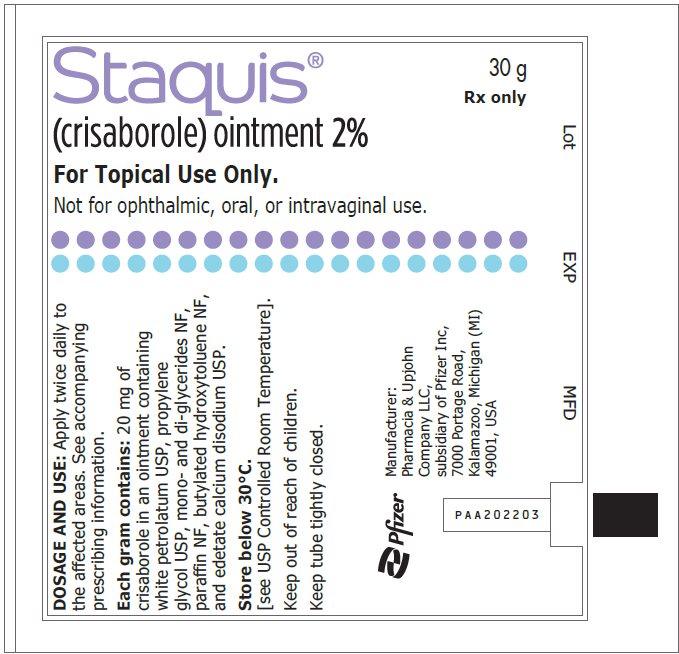 DRUG LABEL: Staquis
NDC: 0009-2211 | Form: OINTMENT
Manufacturer: Pharmacia & Upjohn Company LLC
Category: prescription | Type: HUMAN PRESCRIPTION DRUG LABEL
Date: 20230621

ACTIVE INGREDIENTS: CRISABOROLE 20 mg/1 g
INACTIVE INGREDIENTS: PETROLATUM; PROPYLENE GLYCOL; GLYCERYL MONOSTEARATE; PARAFFIN; BUTYLATED HYDROXYTOLUENE; EDETATE CALCIUM DISODIUM

Staquis® 2%

PRINCIPAL DISPLAY PANEL - Shipping Label – Label 0009-2211-30

Tubo con 30 g

Staquis®

Crisaborol Ungüento 2%

Vía de administración: Cutánea.

Lote:
Caducidad:

PRINCIPAL DISPLAY PANEL - Shipping Label – Carton 0009-2211-30

Staquis®
Crisaborol Ungüento 2%

Caja con tubo con 30 g

Vía de administración: Cutánea.

PRINCIPAL DISPLAY PANEL - Shipping Label – Label 0009-2211-12

Staquis®
30 g
Rx only

(crisaborole) ointment 2%

For Topical Use Only.

Not for ophthalmic, oral, or intravaginal use.

Lot
EXP